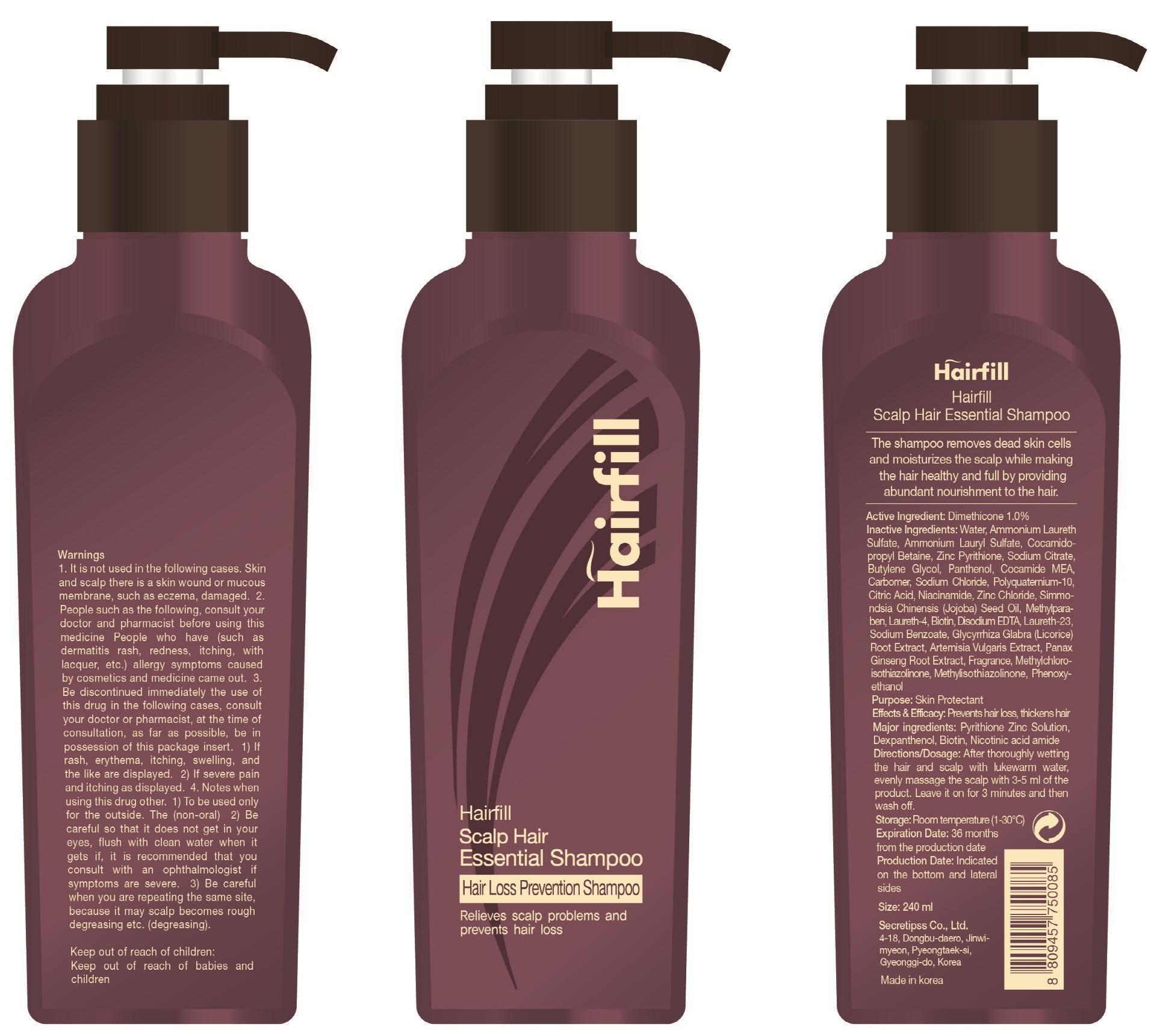 DRUG LABEL: HAIRFILL SCALP HAIR ESSENTIAL
NDC: 69684-320 | Form: SHAMPOO
Manufacturer: SECRETIPSS CO., LTD.
Category: otc | Type: HUMAN OTC DRUG LABEL
Date: 20150609

ACTIVE INGREDIENTS: Dimethicone 2.4 mg/240 mL
INACTIVE INGREDIENTS: WATER; PYRITHIONE ZINC

ACTIVE INGREDIENT

Active Ingredient: Dimethicone 1%

INACTIVE INGREDIENT

Inactive Ingredients: Water, Ammonium Laureth Sulfate, Ammonium Lauryl Sulfate, Cocamidopropyl Betaine, Zinc Pyrithione, Sodium Citrate, Butylene Glycol, Panthenol, Cocamide MEA, Carbomer, Sodium Chloride, Polyquaternium-10, Citric Acid, Niacinamide, Zinc Chloride, Simmondsia Chinensis (Jojoba) Seed Oil, Methylparaben, Laureth-4, Biotin, Disodium EDTA, Laureth-23, Sodium Benzoate, Glycyrrhiza Glabra (Licorice) Root Extract, Artemisia Vulgaris Extract, Panax Ginseng Root Extract, Fragrance, Methylchloroisothiazolinone, Methylisothiazolinone, Phenoxyethanol

PURPOSE

Purpose: Skin Protectant

WARNINGS

Warnings: 1. It is not used in the following cases. Skin and scalp there is a skin wound or mucous membrane, such as eczema, damaged 2. People such as the following, consult your doctor and pharmacist before using this medicine People who have (such as dermatitis rash, redness, itching, with lacquer, etc.) allergy symptoms caused by cosmetics and medicine came out 3. Be discontinued immediately the use of this drug in the following cases, consult your doctor or pharmacist, at the time of consultation, as far as possible, be in possession of this package insert 1) If rash, erythema, itching, swelling, and the like are displayed 2) If severe pain and itching as displayed 4. Notes when using this drug other 1) To be used only for the outside. The (non-oral) 2) Be careful so that it does not get in your eyes, flush with clean water when it gets if, it is recommended that you consult with an ophthalmologist if symptoms are severe. 3) Be careful when you are repeating the same site, because it may scalp becomes rough degreasing etc. (degreasing).

KEEP OUT OF REACH OF CHILDREN

Keep out of reach of babies and children

INDICATIONS & USAGE

Direction & Dosage: After throughly wetting the hair and scalp with lukewarm water, evenly massage the scalp with 3-5 ml of the product. Leave it on for 3 minutes and then wash off.

DOSAGE & ADMINISTRATION

Direction & Dosage: After throughly wetting the hair and scalp with lukewarm water, evenly massage the scalp with 3-5 ml of the product. Leave it on for 3 minutes and then wash off.